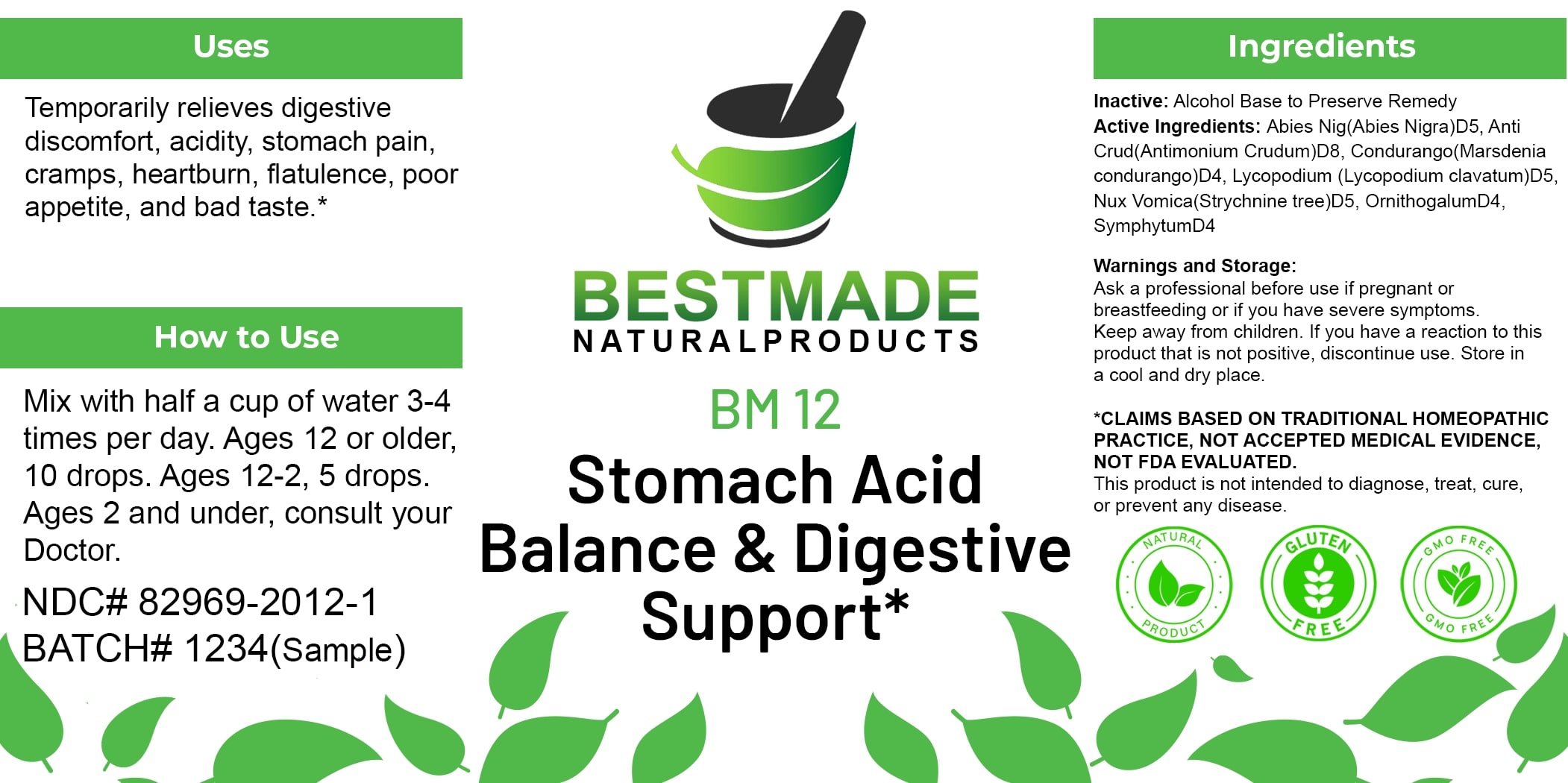 DRUG LABEL: Bestmade Natural Products
NDC: 82969-2012 | Form: LIQUID
Manufacturer: Bestmade Natural Products
Category: homeopathic | Type: HUMAN OTC DRUG LABEL
Date: 20250122

ACTIVE INGREDIENTS: ANTIMONY TRISULFIDE 30 [hp_C]/30 [hp_C]; MARSDENIA CONDURANGO BARK 30 [hp_C]/30 [hp_C]; LYCOPODIUM CLAVATUM SPORE 30 [hp_C]/30 [hp_C]; ORNITHOGALUM UMBELLATUM 30 [hp_C]/30 [hp_C]; COMFREY ROOT 30 [hp_C]/30 [hp_C]; PICEA MARIANA RESIN 30 [hp_C]/30 [hp_C]; STRYCHNOS NUX-VOMICA SEED 30 [hp_C]/30 [hp_C]
INACTIVE INGREDIENTS: ALCOHOL 30 [hp_C]/30 [hp_C]

BM12

DOSAGE AND ADMINISTRATION

How to Use

Mix with half a cup of water 3-4 times per day.

Ages 12 or older: 10 drops
Ages 2-12: 5 drops
Ages 2 and under: Consult your doctor.

INACTIVE INGREDIENT

Ingredients

Inactive: Alcohol Base to Preserve Remedy

Uses

Temporarily relieves digestive discomfort, acidity, stomach pain, cramps, heartburn, flatulence, poor appetite, and bad taste.*

*CLAIMS BASED ON TRADITIONAL HOMEOPATHIC PRACTICE, NOT ACCEPTED MEDICAL EVIDENCE, NOT FDA EVALUATED.
This product is not intended to diagnose, treat, cure, or prevent any disease.

Active Ingredients:

Abies Nig (Abies Nigra) D5
Anti Crud (Antimonium Crudum) D8
Condurango (Marsdenia Condurango) D4
Lycopodium (Lycopodium Clavatum) D5
Nux Vomica (Strychnine Tree) D5
Ornithogalum D4
Symphytum D4

KEEP OUT OF REACH OF CHILDREN

Warnings and Storage

Ask a professional before use if pregnant or breastfeeding or if you have severe symptoms. Keep away from children. If you have a reaction to this product that is not positive, discontinue use. Store in a cool and dry place.

Uses

Temporarily relieves digestive discomfort, acidity, stomach pain, cramps, heartburn, flatulence, poor appetite, and bad taste.*

*CLAIMS BASED ON TRADITIONAL HOMEOPATHIC PRACTICE, NOT ACCEPTED MEDICAL EVIDENCE, NOT FDA EVALUATED.

This product is not intended to diagnose, treat, cure, or prevent any disease.

Warnings and Storage

Ask a professional before use if pregnant or breastfeeding or if you have severe symptoms. Keep away from children. If you have a reaction to this product that is not positive, discontinue use. Store in a cool and dry place.

*CLAIMS BASED ON TRADITIONAL HOMEOPATHIC PRACTICE, NOT ACCEPTED MEDICAL EVIDENCE, NOT FDA EVALUATED.
This product is not intended to diagnose, treat, cure, or prevent any disease.

Entire package label